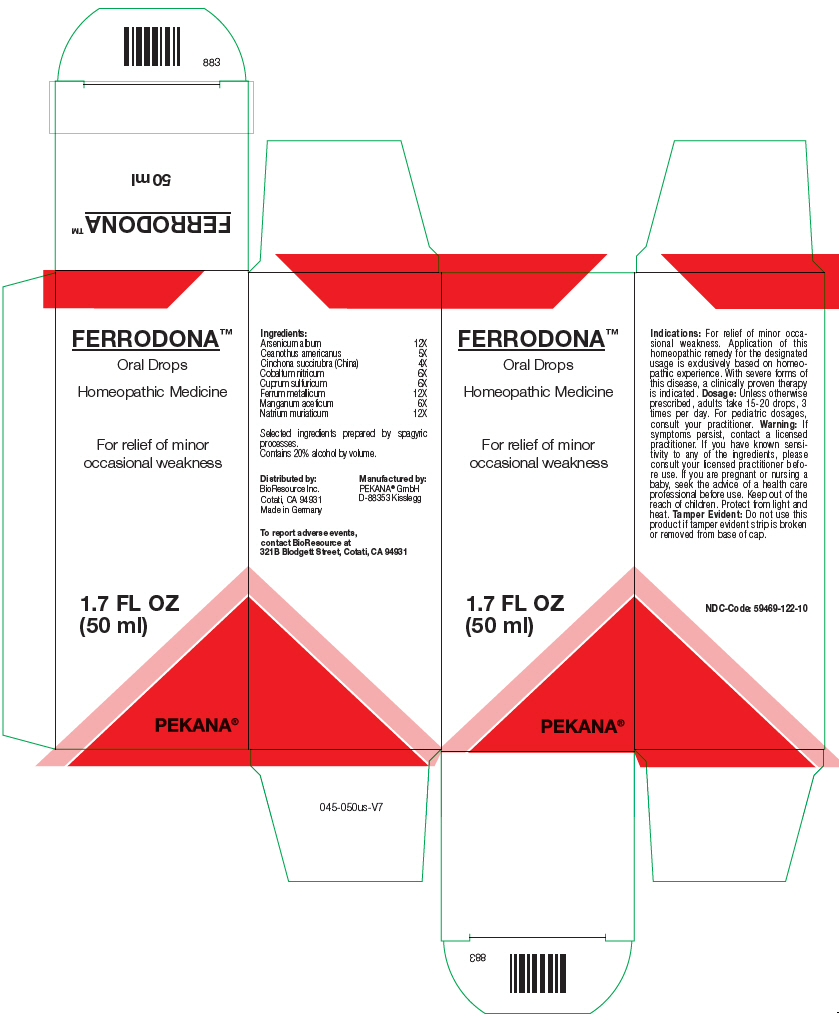 DRUG LABEL: FERRODONNA
NDC: 59469-122 | Form: SOLUTION/ DROPS
Manufacturer: PEKANA Naturheilmittel GmbH
Category: homeopathic | Type: HUMAN OTC DRUG LABEL
Date: 20221214

ACTIVE INGREDIENTS: ARSENIC TRIOXIDE 12 [hp_X]/50 mL; CEANOTHUS AMERICANUS LEAF 5 [hp_X]/50 mL; CINCHONA OFFICINALIS BARK 4 [hp_X]/50 mL; COBALTOUS NITRATE 6 [hp_X]/50 mL; CUPRIC SULFATE 6 [hp_X]/50 mL; IRON 12 [hp_X]/50 mL; MANGANESE ACETATE 6 [hp_X]/50 mL; SODIUM CHLORIDE 12 [hp_X]/50 mL
INACTIVE INGREDIENTS: Water; Alcohol

FERRODONNA™

ACTIVE INGREDIENT

Ingredients:
Arsenicum album | 12X
Ceanothus americanus | 5X
Cinchona succirubra (China) | 4X
Cobaltum nitricum | 6X
Cuprum sulfuricum | 6X
Ferrum metallicum | 12X
Manganum aceticum | 6X
Natrium muriaticum | 12X

INACTIVE INGREDIENT

Selected ingredients prepared by spagyric processes.

Contains 20% alcohol by volume.

Indications

PURPOSE

For relief of minor occasional weakness. Application of this homeopathic remedy for the designated usage is exclusively based on homeopathic experience. With severe forms of this disease, a clinically proven therapy is indicated.

Dosage

Unless otherwise prescribed, adults take 15-20 drops, 3 times per day. For pediatric dosages, consult your practitioner.

Warning

ASK DOCTOR

If symptoms persist, contact a licensed practitioner. If you have known sensitivity to any of the ingredients, please consult your licensed practitioner before use. If you are pregnant or nursing a baby, seek the advice of a health care professional before use.

Keep out of the reach of children.

STORAGE AND HANDLING

Protect from light and heat.

Tamper Evident

Do not use this product if tamper evident strip is broken or removed from base of cap.

QUESTIONS

To report adverse events, contact BioResource at 321B Blodgett Street, Cotati, CA 94931

Manufactured by:
PEKANA® GmbH
D-88353 Kisslegg

Distributed by:
BioResource Inc.
Cotati, CA 94931

PRINCIPAL DISPLAY PANEL - 50 ml Bottle Box

FERRODONA™
Oral Drops

Homeopathic Medicine

For relief of minor
occasional weakness

1.7 FL OZ
(50 ml)

PEKANA®